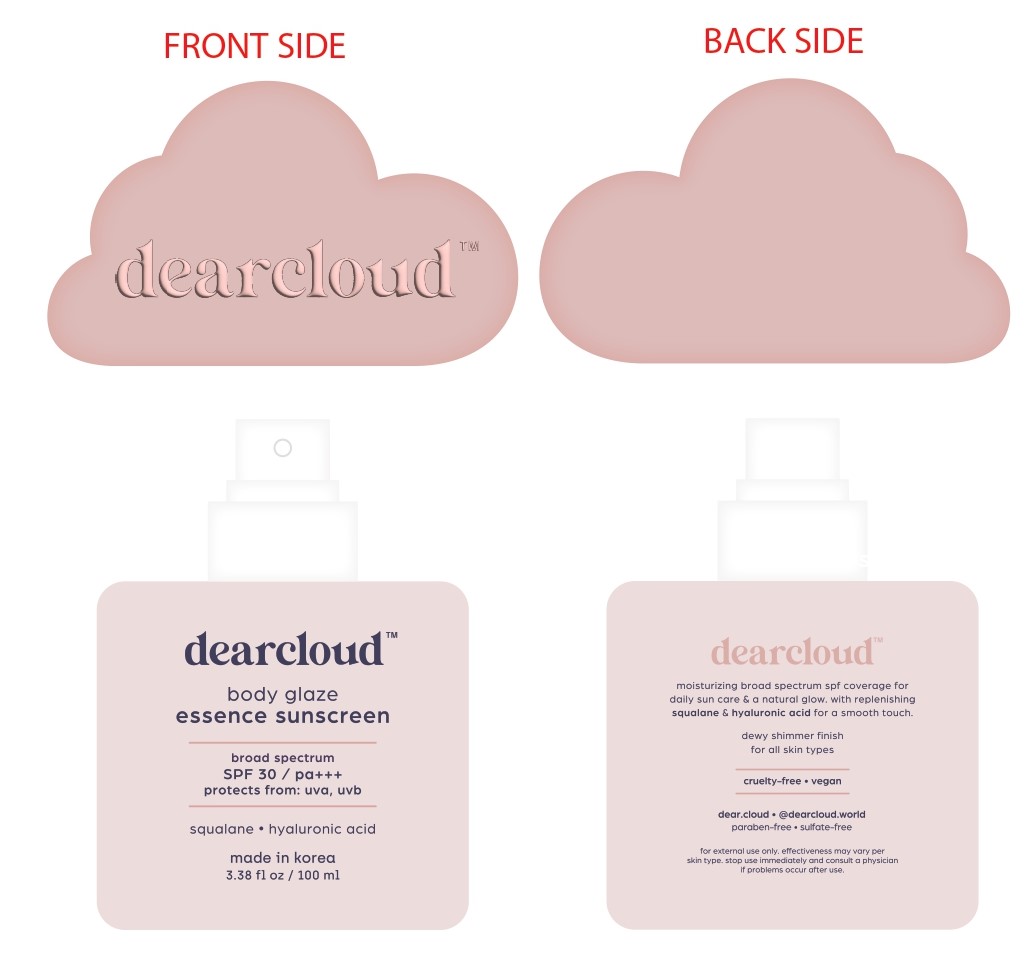 DRUG LABEL: Body Glaze Essence Sunscreen
NDC: 84326-824 | Form: SPRAY
Manufacturer: RBGROUP Co., Ltd
Category: otc | Type: HUMAN OTC DRUG LABEL
Date: 20251021

ACTIVE INGREDIENTS: OCTOCRYLENE 9.5 g/100 g; AVOBENZONE 2.8 g/100 g; OCTISALATE 4.7 g/100 g; HOMOSALATE 7.2 g/100 g
INACTIVE INGREDIENTS: ETHYLHEXYLGLYCERIN; ARGININE; CAPRYLYL METHICONE; 1,2-HEXANEDIOL; BEHENYL ACRYLATE POLYMER; SORBITAN OLIVATE; SQUALANE; NIACINAMIDE; CETEARYL GLUCOSIDE; POLYACRYLATE CROSSPOLYMER-6; ALPHA-TOCOPHEROL ACETATE; BUTYLENE GLYCOL; CAPRYLYL GLYCOL; RICE GERM; STEARETH-30; TOCOPHEROL; DIPROPYLENE GLYCOL; CI 77491; XANTHAN GUM; CETEARYL ALCOHOL; GLYCERYL STEARATE SE; WATER; DICAPRYLYL CARBONATE; PANTHENOL; ADENOSINE; POLYSORBATE 80; BENZYL GLYCOL; PRICKLY PEAR FRUIT; SODIUM HYALURONATE; METHYLPROPANEDIOL; POLYMETHYLSILSESQUIOXANE (4.5 MICRONS)

84326-824 Body Glaze Essence Sunscreen

ACTIVE INGREDIENT

Avobenzone 2.8%

Homosalate 7.2%

Octisalate 4.7%

Octocrylene 9.5%

PURPOSE

Sunscreen

INDICATIONS AND USAGE

● Helps prevent sunburn.

● If used as directed with other sun protection measures (see Directions), decreases the risk of skin cancer and early skin aging caused by the sun.

WARNINGS

For external use only

DO NOT USE

● on damaged or broken skin

WHEN USING

this product ● keep out of eyes. Rinse with water to remove.

KEEP OUT OF REACH OF CHILDREN

If swallowed, get medical help or contact a Poison Control Center right away.

WARNINGS

● Use only as directed. Intentional misuse by deliberately concentrating and inhaling the contents can be harmful or fatal.

Directions

● Spray liberally and spread evenly by hand 15 minutes before sun exposure

● Apply to all skin exposed to the sun

● Do not spray directly into face

● Spray on hands and then apply. Rub in.

● If bothersome dryness or peeling occurs, reduce application to once a day or every other day

● Do not apply in windy conditions

● Use in a well-ventilated area

● Reapply at least every 2 hours.

● Children under 6 months of age: Ask a doctor.

● Sun Protection Measures. Spending time in the sun increases your risk of skin cancer and early skin aging. ● To decrease this risk, regularly use a sunscreen with a Broad Spectrum SPF of 15 or higher and other sun protection measures including: ● Limit time in the sun, especially from 10 a.m.-2 p.m. ● Wear long-sleeve shirts, pants, hats, and sunglasses.

INACTIVE INGREDIENT

Water, Butyloctyl Salicylate, Niacinamide, Caprylyl Methicone, Dipropylene Glycol, Cetearyl Glucoside, Poly C10-30 Alkyl Acrylate, Sorbitan Olivate, Polysorbate 80, Benzyl Glycol, Cetearyl Alcohol, Glyceryl Stearate SE, Cetyl PEG/PPG-10/ Dimethicone, Polymethylsilsesquioxane, Dicaprylyl Carbonate, Panthenol, Acrylates/C10-30 Alkyl Acrylate Crosspolymer, Arginine, Methylpropanediol, Ethylhexylglycerin, Squalane, Polyacrylate Crosspolymer-6, Tocophyeryl Acetate, Butylene Glycol, Caprylyl Glycol, Xanthan Gum, Hydroxypropyl Methylcellulose Stearoxy Ether, 1,2-Hexanediol, Adenosine, Oryza Sativa (Rice) Extract, Opuntia Ficus-Indica Fruit Extract, Steareth-30, Tocopherol, Sodium Hyaluronate, Fragrance, CI 77019, CI 77491